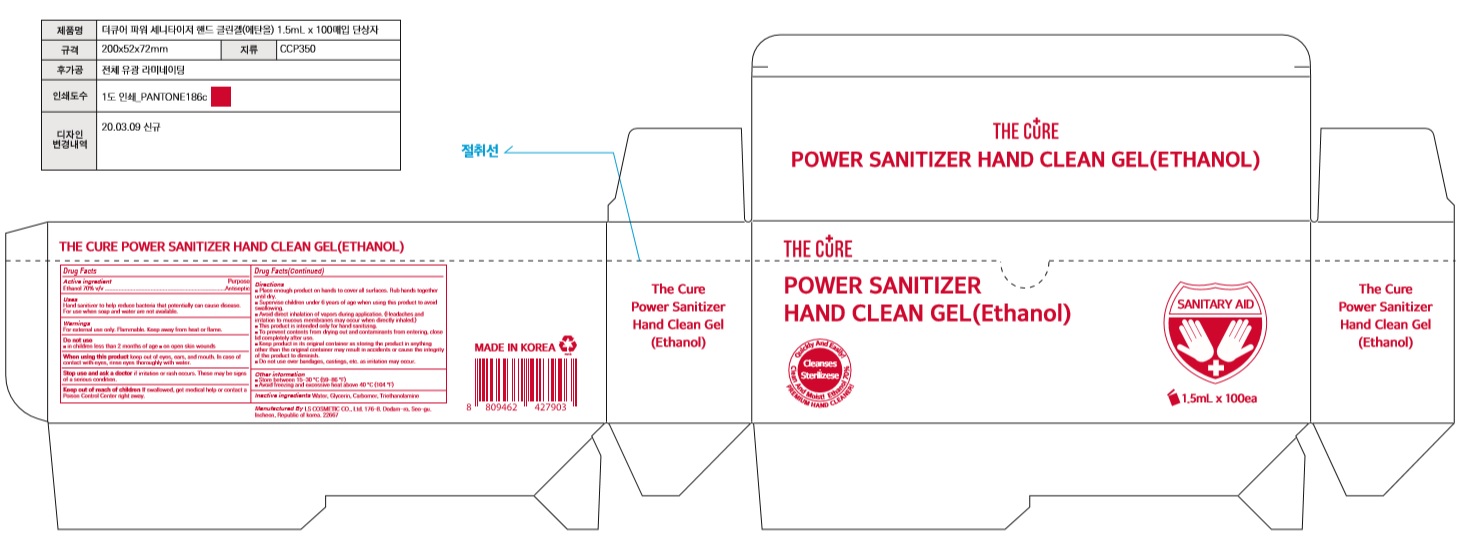 DRUG LABEL: THE CURE POWER SANITIZER HAND CLEAN Gel(Ethanol)
NDC: 59545-0715 | Form: GEL
Manufacturer: LS COSMETIC CO.,LTD.
Category: otc | Type: HUMAN OTC DRUG LABEL
Date: 20200413

ACTIVE INGREDIENTS: ALCOHOL 1.05 mL/1.5 mL
INACTIVE INGREDIENTS: GLYCERIN; CARBOMER HOMOPOLYMER, UNSPECIFIED TYPE; WATER; TROLAMINE

THE CURE POWER SANITIZER HAND CLEAN Gel(Ethanol) : 59545-0715